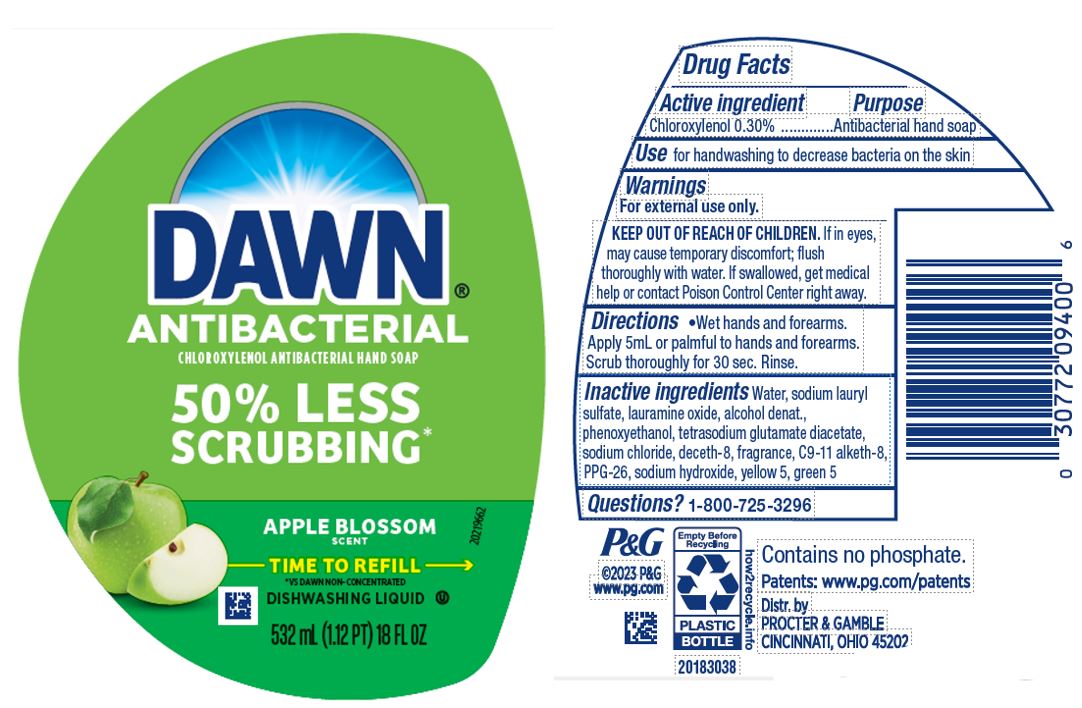 DRUG LABEL: Dawn Ultra Antibacterial Hand
NDC: 37000-616 | Form: SOAP
Manufacturer: The Procter & Gamble Manufacturing Company
Category: otc | Type: HUMAN OTC DRUG LABEL
Date: 20250317

ACTIVE INGREDIENTS: CHLOROXYLENOL 0.3 g/100 mL
INACTIVE INGREDIENTS: C9-11 PARETH-8; ALCOHOL; FD&C YELLOW NO. 5; D&C GREEN NO. 5; WATER; SODIUM LAURYL SULFATE; LAURAMINE OXIDE; PHENOXYETHANOL; SODIUM CHLORIDE; PPG-26; DECETH-8; SODIUM HYDROXIDE; TETRASODIUM GLUTAMATE DIACETATE

Dawn® Ultra Antibacterial Hand
Apple Blossom® Scent

Drug Facts

Active ingredient

Chloroxylenol 0.30%

Purpose

Antibacterial hand soap

Use

- for handwashing to decrease bacteria on the skin

Warnings

For external use only

Keep out of reach of children. In case of accidental ingestion, drink a glass of water to dilute. If eye contact occurs, rinse thoroughly with water.

Directions

- wet hands and forearms. Apply 5 ml or palmful to hands and forearms. Scrub thoroughly for 30 sec. and rinse.

Inactive ingredients

Water, sodium lauryl sulfate, lauramine oxide, alcohol denat., phenoxyethanol, tetrasodium glutamate diacetate, sodium chloride, deceth-8, fragrance, C9-11 alketh-8, PPG-26, sodium hydroxide, yellow 5, green 5

Questions?

1-800-725-3296

Distributed by PROCTER & GAMBLE,
CINCINNATI, OH 45202

PRINCIPAL DISPLAY PANEL - 532 mL (1.12PT) 18 FL OZ Bottle Label

DAWN®
ANTIBACTERIAL

CHLOROXYLENOL ANTIBACTERIAL HAND SOAP

APPLE BLOSSOM SCENT

VS.DAWN NON-CONCENTRATED

DISHWASHING LIQUID

532 mL (1.12 PT) 18 FL OZ